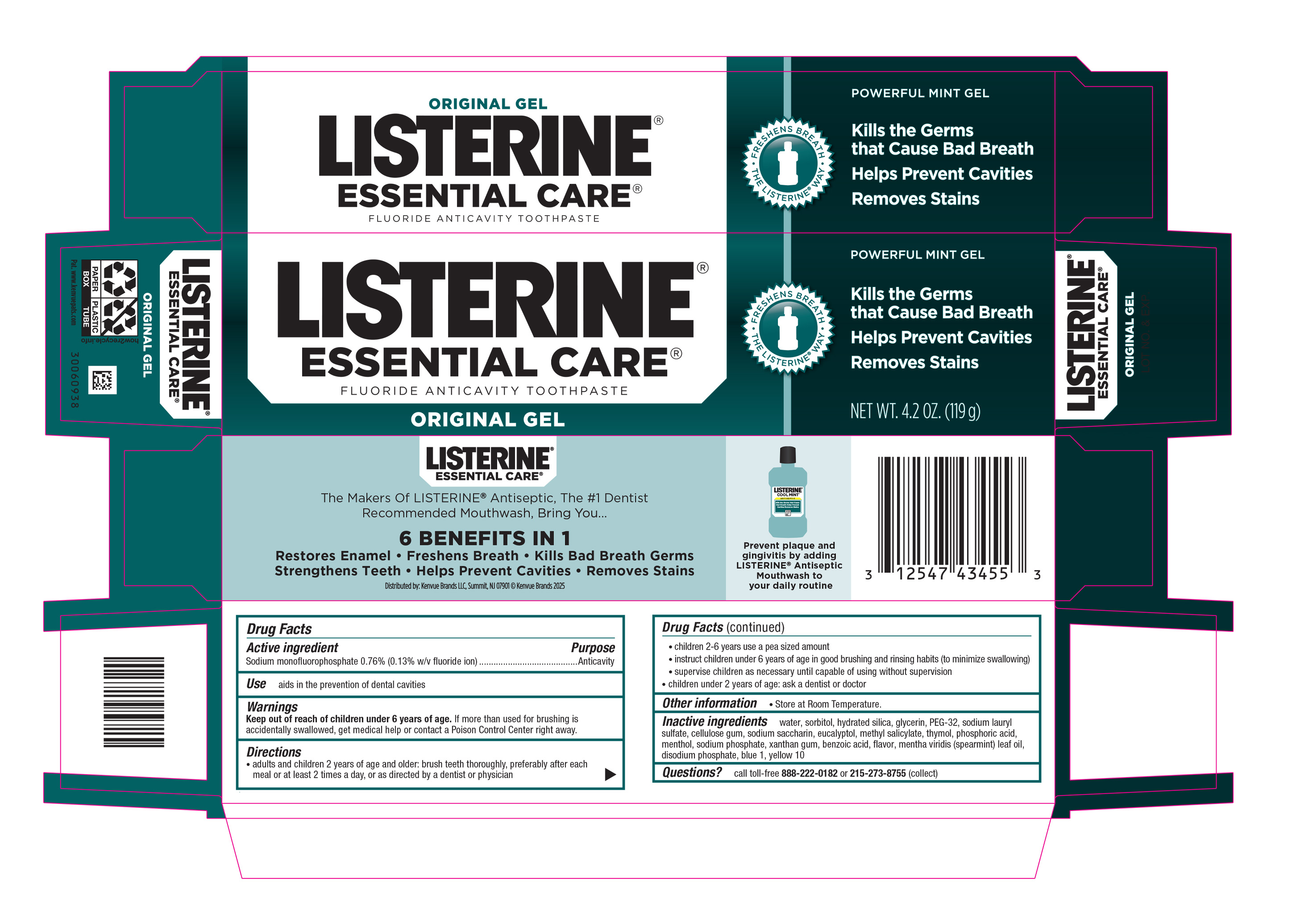 DRUG LABEL: Listerine Essential Care
NDC: 69968-0701 | Form: GEL, DENTIFRICE
Manufacturer: Kenvue Brands LLC
Category: otc | Type: HUMAN OTC DRUG LABEL
Date: 20251010

ACTIVE INGREDIENTS: SODIUM MONOFLUOROPHOSPHATE 1.3 mg/1 g
INACTIVE INGREDIENTS: WATER; SORBITOL; HYDRATED SILICA; GLYCERIN; POLYETHYLENE GLYCOL 1600; SODIUM LAURYL SULFATE; CARBOXYMETHYLCELLULOSE SODIUM, UNSPECIFIED; SACCHARIN SODIUM; EUCALYPTOL; METHYL SALICYLATE; THYMOL; PHOSPHORIC ACID; MENTHOL, UNSPECIFIED FORM; SODIUM PHOSPHATE; XANTHAN GUM; BENZOIC ACID; SPEARMINT OIL; SODIUM PHOSPHATE, DIBASIC, ANHYDROUS; FD&C BLUE NO. 1; D&C YELLOW NO. 10

LISTERINE® ESSENTIAL CARE® GEL

Drug Facts

Active ingredient

Sodium monofluorophosphate 0.76% (0.13% w/v fluoride ion)

Purpose

Anticavity

Use

aids in the prevention of dental cavities

Warnings

Keep out of reach of children under 6 years of age. If more than used for brushing is accidently swallowed, get medical help or contact a Poison Control Center right away.

Directions

- adults and children 2 years of age and older: brush teeth thoroughly, preferably after each meal or at least 2 times a day, or as directed by a dentist or physician.
  - children 2-6 years use a pea sized amount
  - instruct children under 6 years of age in good brushing and rinsing habits (to minimize swallowing)
  - supervise children as necessary until capable of using without supervision.
- children under 2 years of age: ask a dentist or doctor

Other information

- Store at Room Temperature.

Inactive ingredients

water, sorbitol, hydrated silica, glycerin, PEG-32, sodium lauryl sulfate, cellulose gum, sodium saccharin, eucalyptol, methyl salicylate, thymol, phosphoric acid, menthol, sodium phosphate, xanthan gum, benzoic acid, flavor, mentha viridis (spearmint) leaf oil, disodium phosphate, blue 1, yellow 10

Questions?

call toll-free 888-222-0182 or 215-273-8755 (collect)

Distributed by: Kenvue Brands LLC, Summit, NJ 07901

PRINCIPAL DISPLAY PANEL - 119 g Tube Carton

LISTERINE®
ESSENTIAL CARE®
FLUORIDE ANTICAVITY TOOTHPASTE
ORIGINAL GEL

- FRESHENS BREATH
- THE LISTERINE® WAY

POWERFULL MINT GEL
Kills the Germs
that Cause Bad Breath
Helps Prevent Cavities
Removes Stains
NET WT. 4.2 OZ. (119 g)